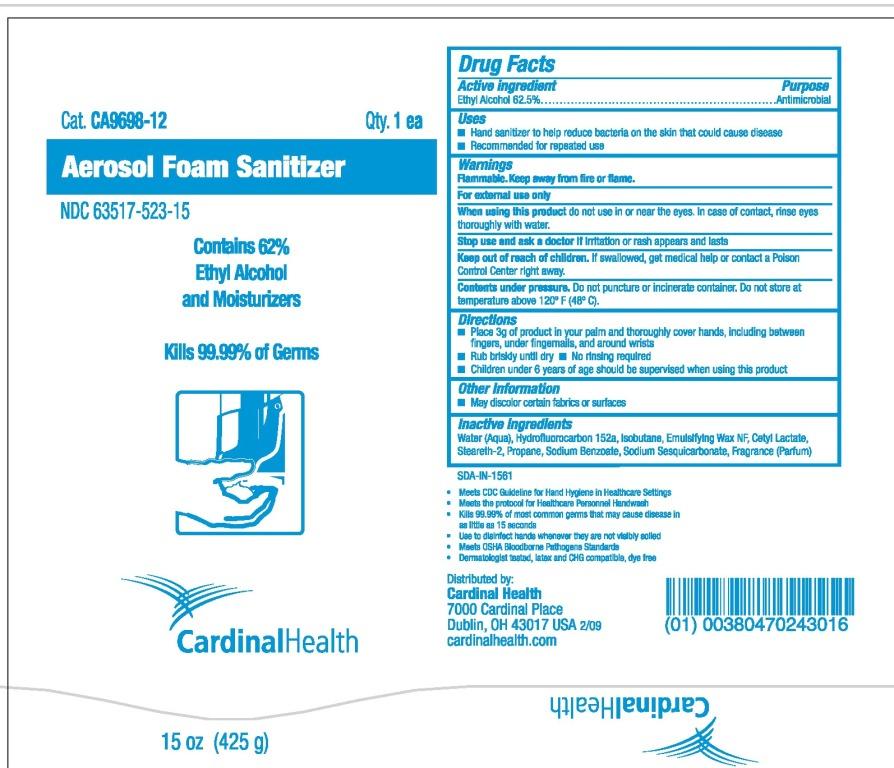 DRUG LABEL: Cardinal Health Sanitizer
NDC: 63517-523 | Form: AEROSOL, FOAM
Manufacturer: Cardinal Health
Category: otc | Type: HUMAN OTC DRUG LABEL
Date: 20110224

ACTIVE INGREDIENTS: ALCOHOL 0.625 mg/1 mg
INACTIVE INGREDIENTS: WATER; 1,1-DIFLUOROETHANE; STEARETH-2; SODIUM BENZOATE

PACKAGE LABEL

Cardinal Health Aerosol Foam Sanitizer

Directions

- Place enough product in your palm to thoroughly cover your hands
- Rub hands together briskly until dry
- Children under 6 years of age should be supervised when using this product

DOSAGE AND ADMINISTRATION

Apply approx. 3g

PURPOSE

Antimicrobial

Keep out of reach of children.

Warnings Flammable.
Keep away from fire or flame.
For external use only When using this product do not use in or near the eyes. In case of contact, rinse eyes thoroughly with water.
Stop use and ask a doctor if irritation or rash appears and lasts
Keep out of reach of children. If swallowed, get medical help or contact a Poison Control Center right away.
Contents under pressure. Do not puncture or incinerate container. Do not store at temperature above 120°F (48°C).

Active ingredient Ethyl alcohol 62.5%

INACTIVE INGREDIENT

Inactive Ingredients Water (Aqua), Hydrofluorocarbon 152a, Isobutane, Emulsifying Wax NF, Cetyl Lactate, Steareth-2, Propane, Sodium Benzoate, Sodium Sesquicarbonate, Fragrance (Parfum)